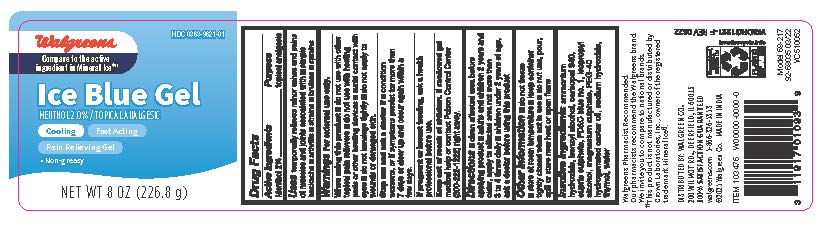 DRUG LABEL: Walgreens Ice Blue Gel
NDC: 0363-9621 | Form: GEL
Manufacturer: Walgreens Company
Category: otc | Type: HUMAN OTC DRUG LABEL
Date: 20241217

ACTIVE INGREDIENTS: MENTHOL 2 g/100 g
INACTIVE INGREDIENTS: THYMOL; CARBOMER 940; BENZYL ALCOHOL; CUPRIC SULFATE; MAGNESIUM SULFATE, UNSPECIFIED; WATER; AMMONIA; POLYOXYL 40 HYDROGENATED CASTOR OIL; ISOPROPYL ALCOHOL; SODIUM HYDROXIDE; FD&C BLUE NO. 1

Walgreens Ice Blue Gel

ACTIVE INGREDIENT

Menthol 2%

PURPOSE

Topical analgesic

Uses

Temporarily relieves minor aches and pains of muscles and joints associated with

- simple backache
- arthritis
- strains
- bruises
- sprains

WARNINGS

For external use only

- Do not use with other topical pain relievers
- Do not use with heating pads or other heating devices
- Avoid contact with eyes
- Do not bandage tightly
- Do not apply to wounds or damage skin

Stop use and ask a doctor if:

Condition worsens, or if symptoms persist for more than 7 day or clear up and occur again withing a few days

If pregnant or breastfeeding

Ask a health professional before use

Keep out of reach of children

If swallowed get medical help or contact Poison Control Center (800-222-1222) right away

Directions

- Clean affected area before applying product
- Adults and children 2 years and older, apply to the affected area not more than 3 to 4 times daily
- Children under 2 years of age, ask a doctor before using this product

Other Information

- Do not freeze
- Store at room temperatiure
- Keep container tightly closed when not in use
- do not use, pour, spill or store near heat or open flame

Inactive Ingredients

Ammonium hydroxide, benzyl alcohol, carbopol 940, cupric sulphate, FD&C blue no.1, isopropyl alcohol, magnesium sulphate, PEG-40, hydrogenated castor oil, sodium hydroxide, thymol, water